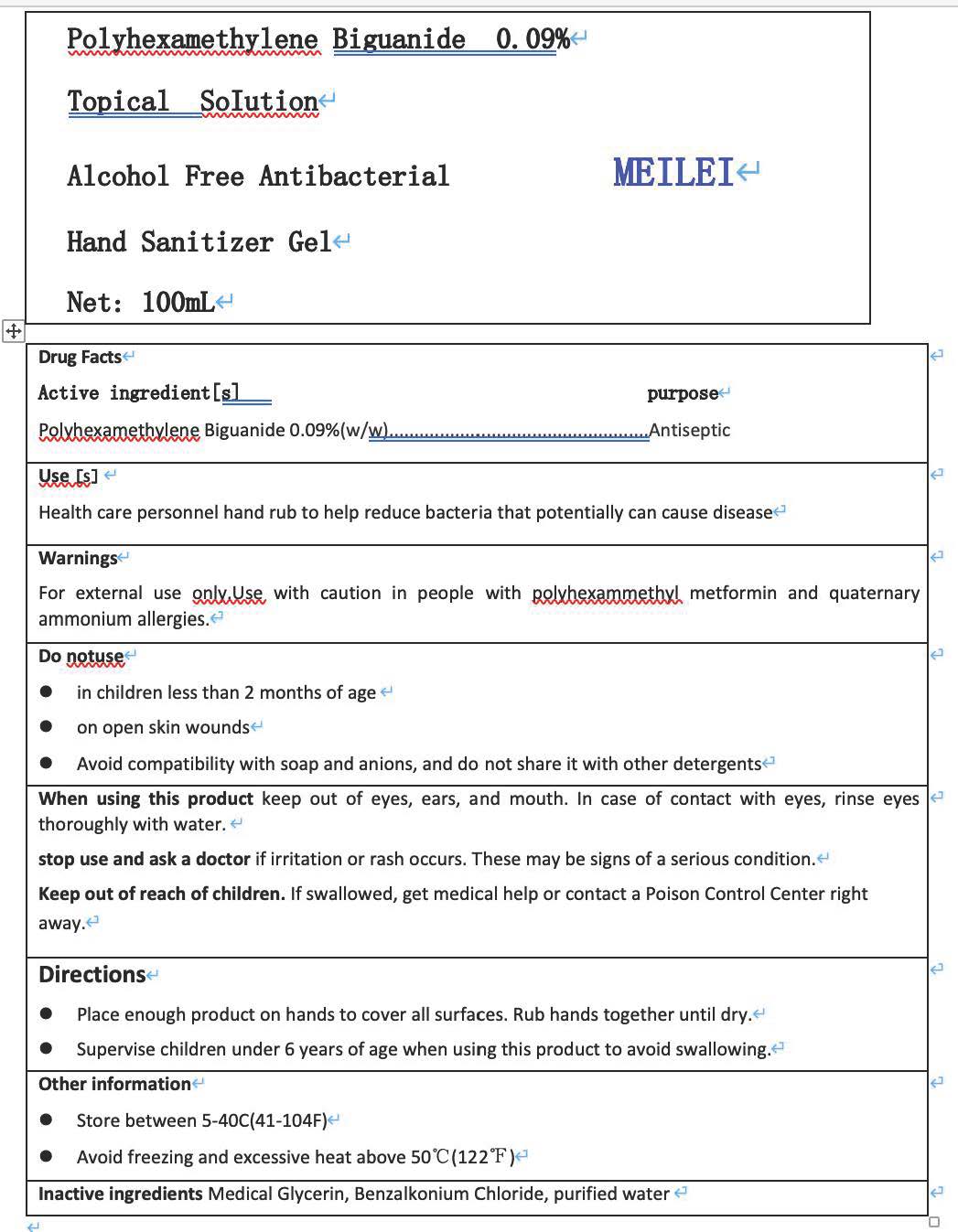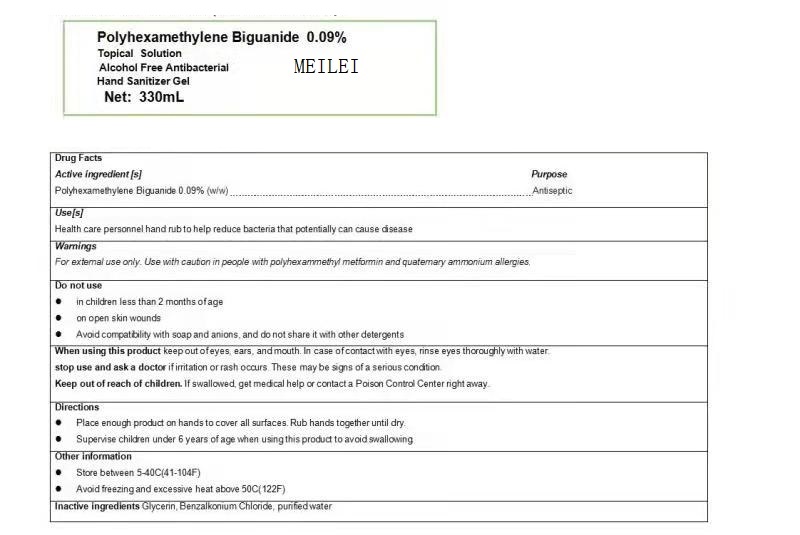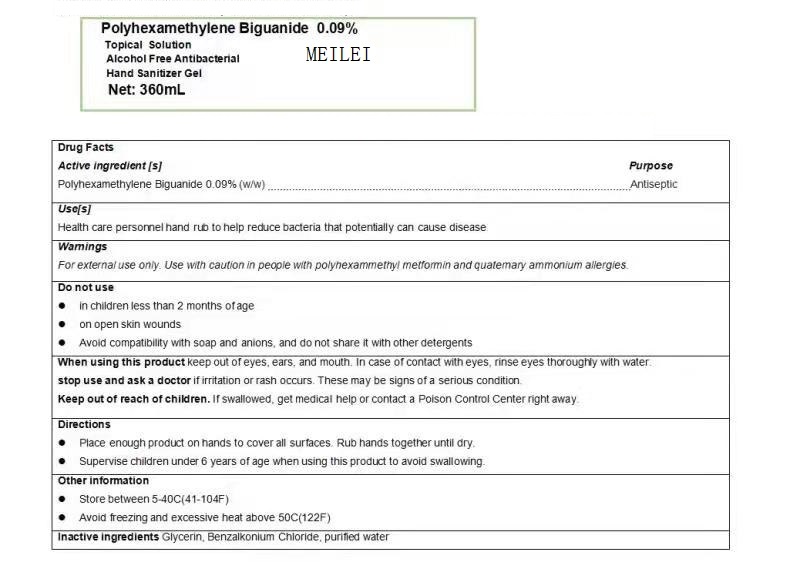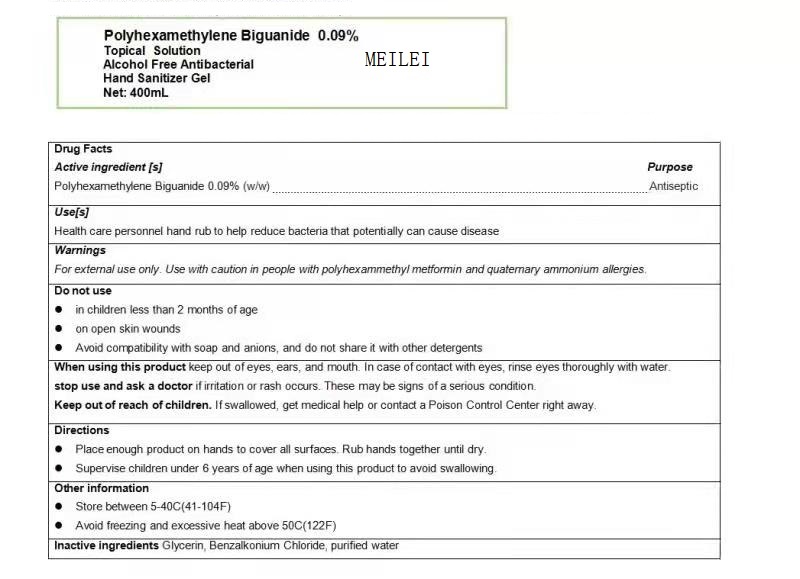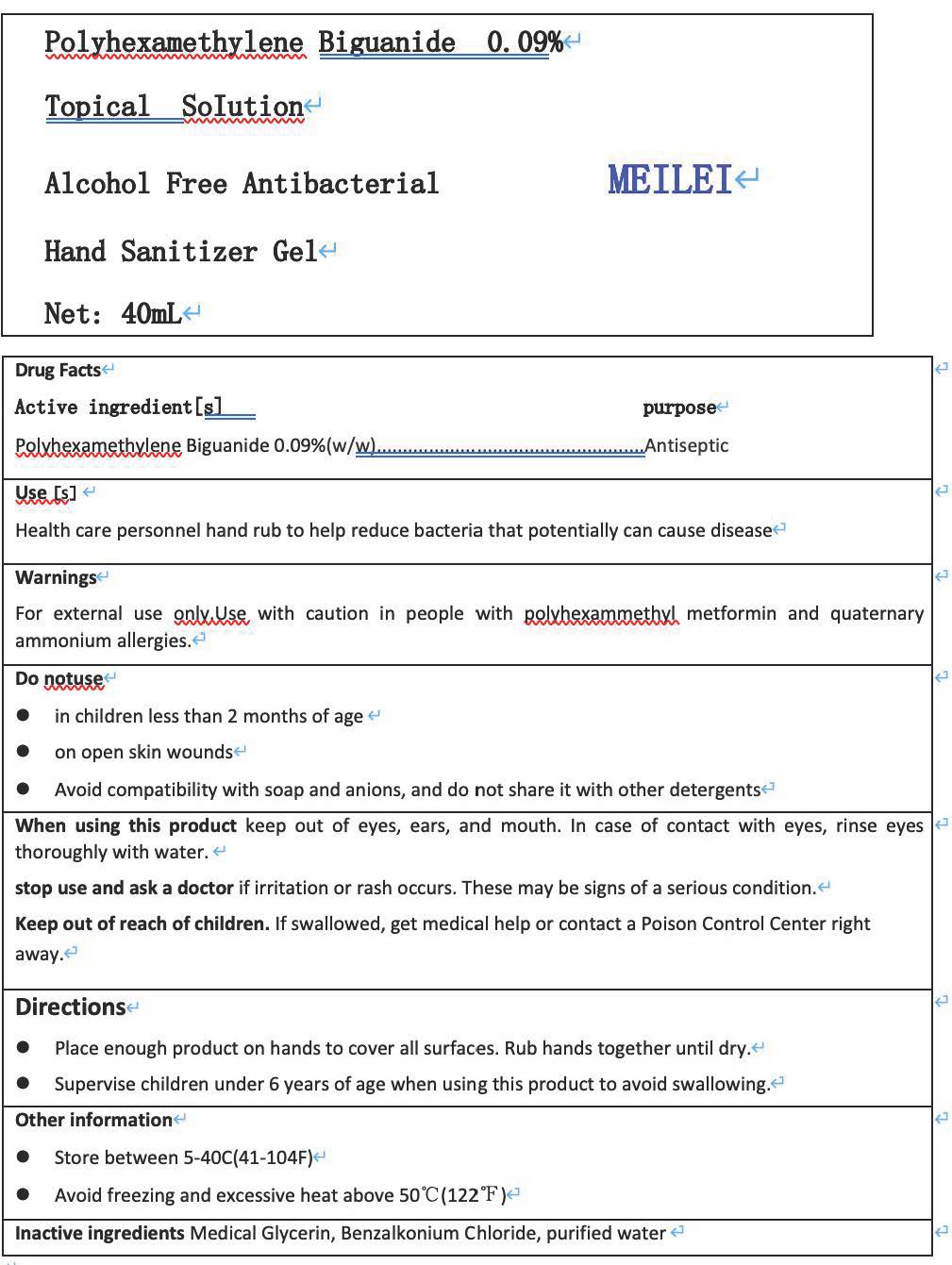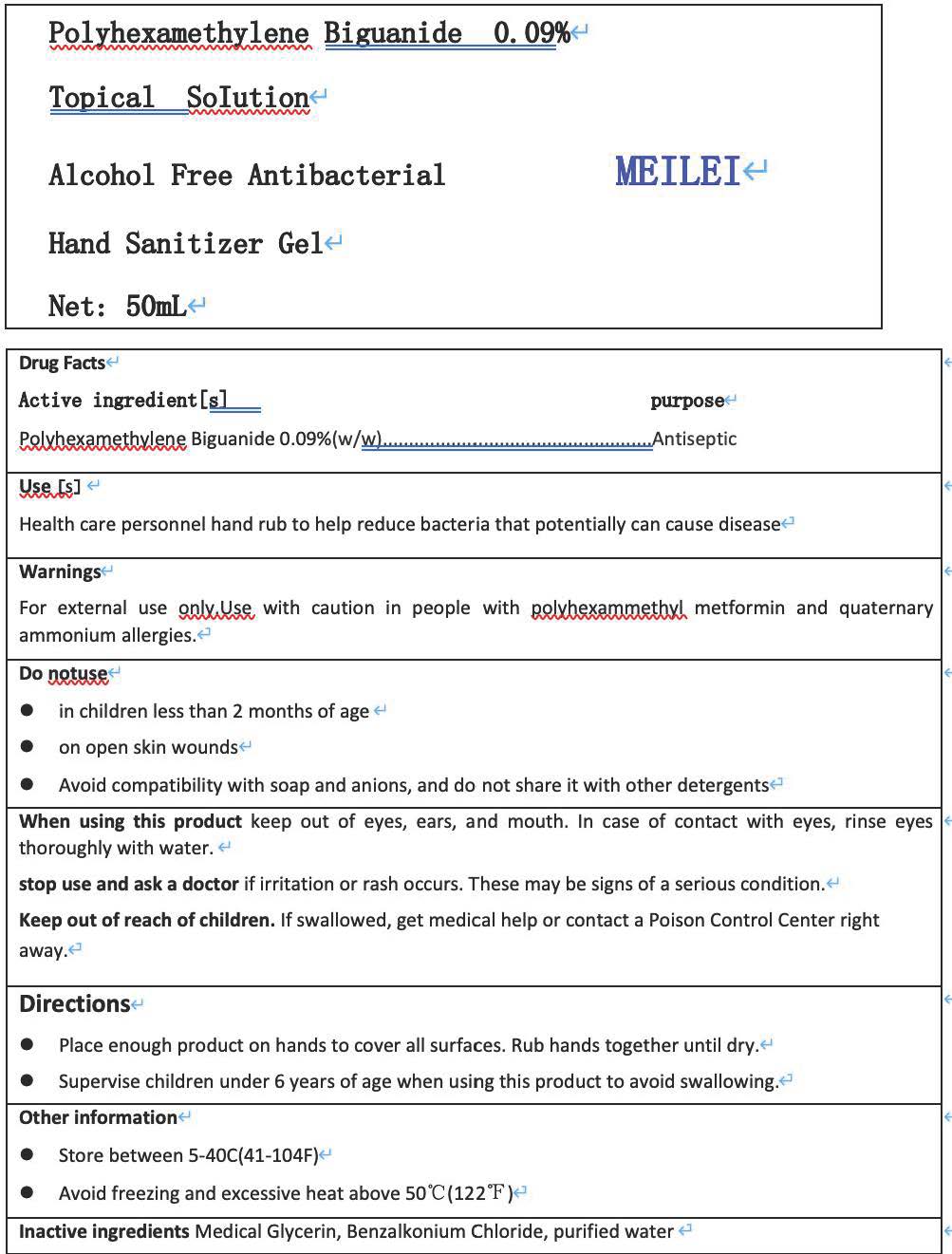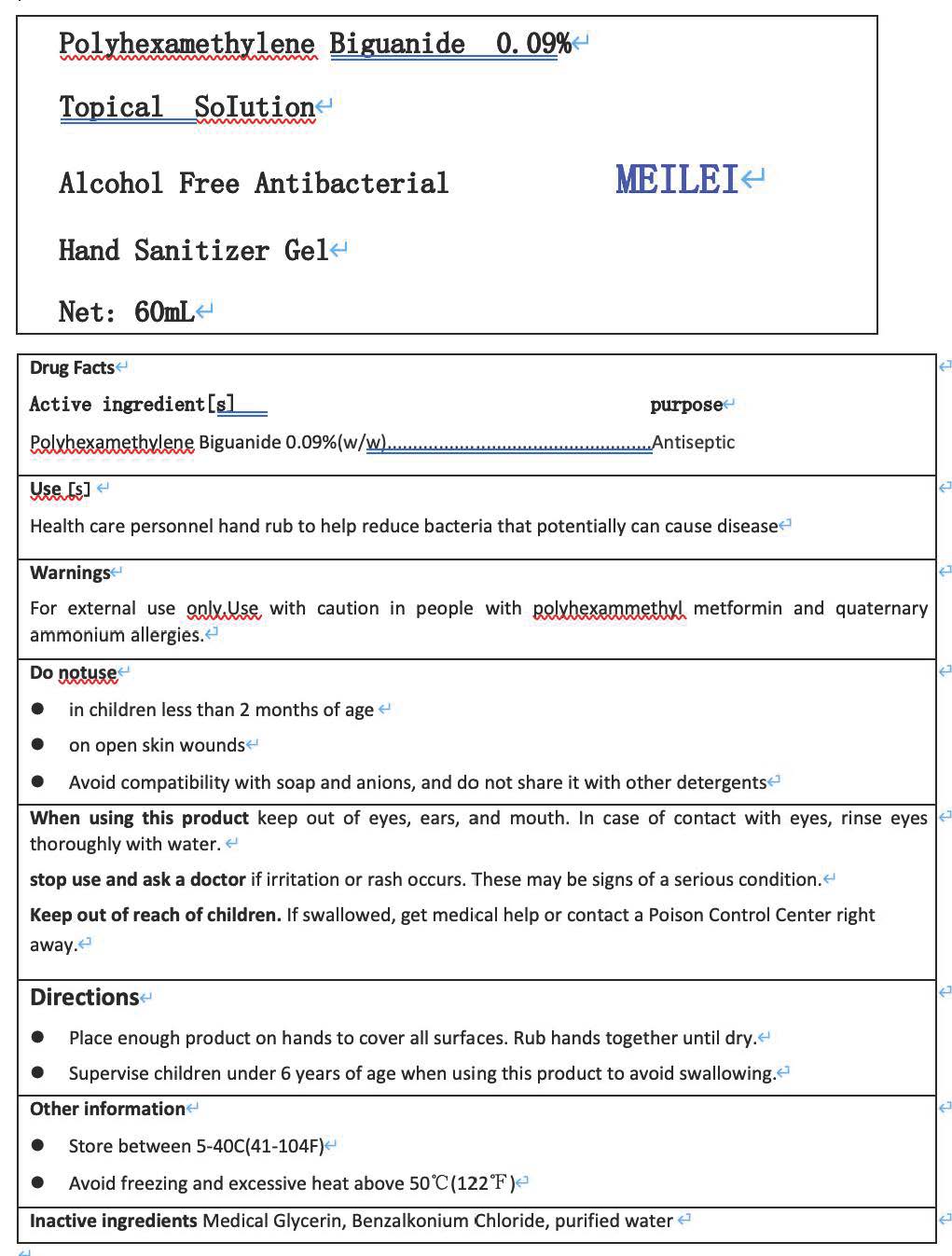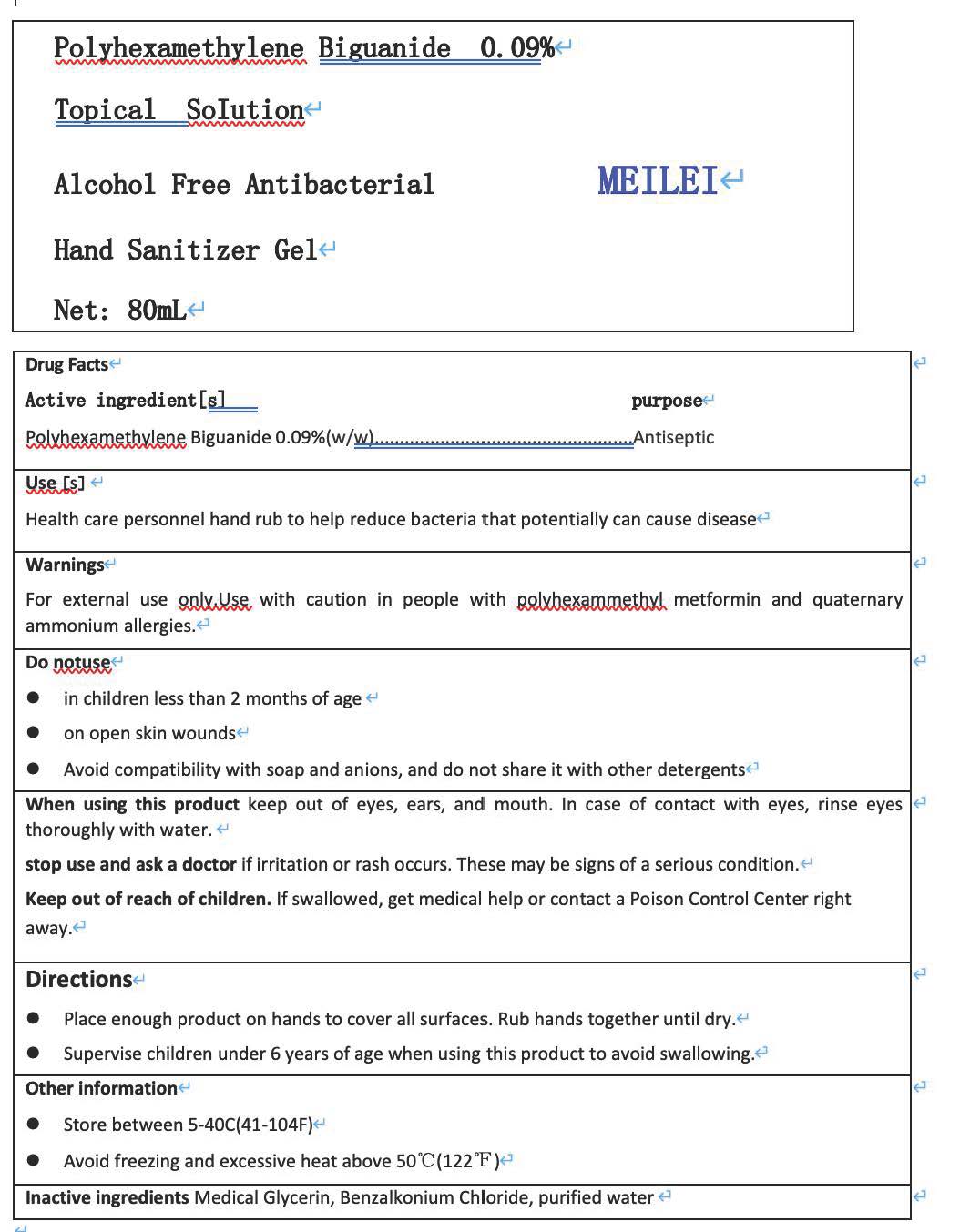 DRUG LABEL: Alcohol Free Antibacterial Hand Sanitizer
NDC: 82658-002 | Form: GEL
Manufacturer: Ningbo Meilei Electrical Appliance Co.,LTD
Category: otc | Type: HUMAN OTC DRUG LABEL
Date: 20220308

ACTIVE INGREDIENTS: POLIHEXANIDE 9 g/10000 g
INACTIVE INGREDIENTS: BENZALKONIUM CHLORIDE; WATER; GLYCERIN

ACTIVE INGREDIENT

Polyhexamethylene biguanide 0.09% (w/w)

INACTIVE INGREDIENT

Medical Glycerin，Benzalkonium Chloride，Purified water

PURPOSE

Health care personnel hand rub to help reduce bacteria that potentially can cause disease.

WARNINGS

For external use only.Use with caution in people with polxhexammethyl metformin and quaternary ammonium allergies.

DO NOT USE

Do notuse in children less than 2 months of age
Do notuse on open skin wounds
Avoid compatibility with soap and anions, and do not share it with other detergents

When using this product keep out of eyes， ears,and mouth. In case of contact with eyes, rinse eyesthoroughly with water.

stop use and ask a doctor if irritation or rash occurs. These may be signs of a serious condition.

Keep out of reach of children. If swallowed, get medical help or contact a Poison Control Center rightaway.

INDICATIONS AND USAGE

Antiseptic

Place enough product on hands to cover all surfaces.Rub hands together until dry.
Supervise children under 6 years of age when using this product to avoid swallowing.

DOSAGE AND ADMINISTRATION

Place enough product on hands to cover all surfaces.Rub hands together until dry.
Supervise children under 6 years of age when using this product to avoid swallowing.

STORAGE AND HANDLING

Store between 5-40℃(41-104℉)
Avoid freezing and excessive heat above 50℃(122℉)